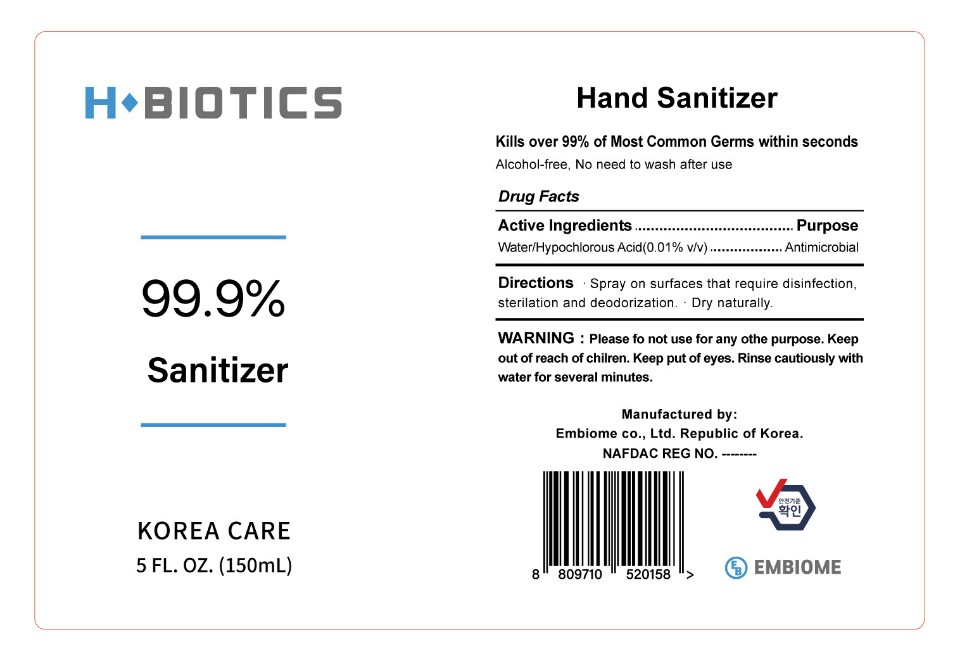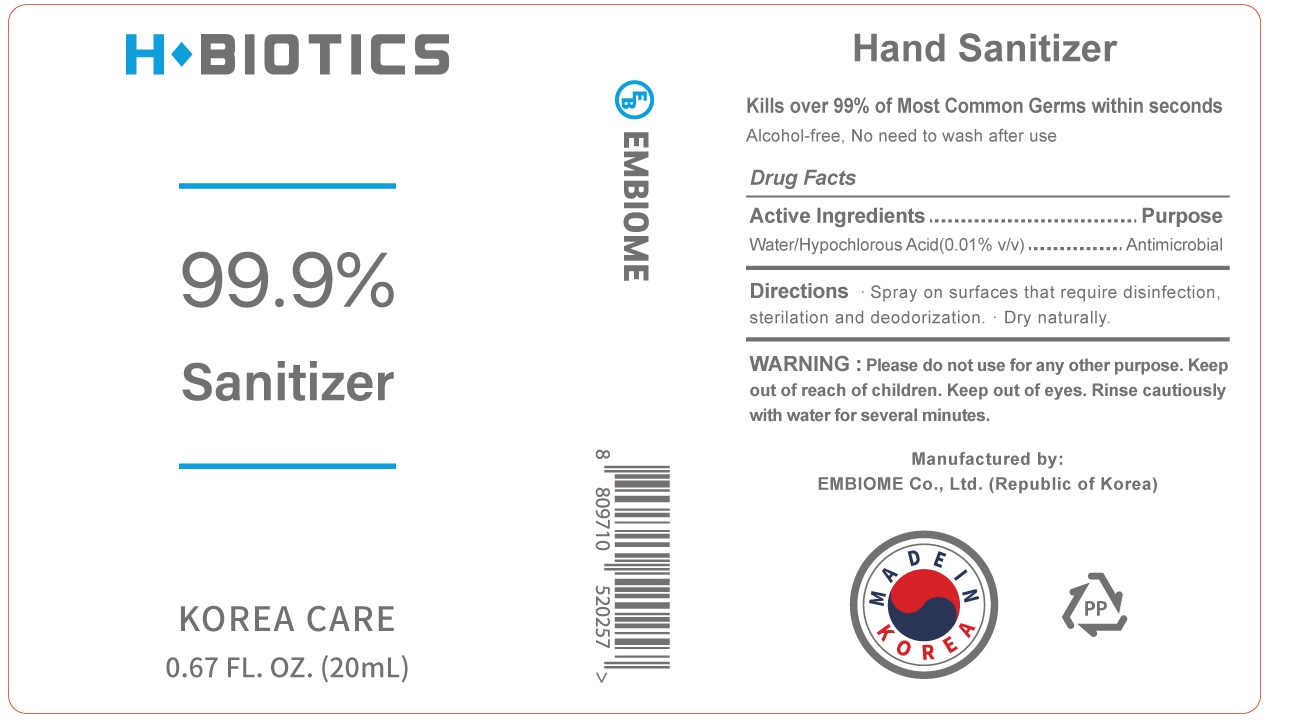 DRUG LABEL: H BIOTICS
NDC: 79045-301 | Form: LIQUID
Manufacturer: EMBIOME Co., Ltd.
Category: otc | Type: HUMAN OTC DRUG LABEL
Date: 20211111

ACTIVE INGREDIENTS: HYPOCHLOROUS ACID 0.01 g/100 mL
INACTIVE INGREDIENTS: WATER 99.9 mL/100 mL

sanitizer

Active Ingredient

Hypochlorous ACID

PURPOSE

ANTIMICROBIAL

Inactive

WATER

Stop use

if irritationor rash occurs. These may be signs of a serious contion.

ask a doctor.

if irritationor rash occurs. These may be signs of a serious contion.

Warnings

Please do not use for any other purpose

keep put of eyes.

rinse cautiously with water of several minutes.

uses

Hand sanitizer to decrease bacteria on the skin that could cause disease

When using this product

kills over 99% of most common germs.

Keep out of reach of children.

Other information

Store between 33.8~86'F
Avoid freezing and excessive heat

directions

spray on surfaces that require disinfection, sterilation and dedorization.

dry naturally.

Place enough product on hands to cover all surfaces. Rub hands together until dry.

Supervise children under 6 years of age when using this product to avoid swallowing.

LABEL

79045-301-01

79045-301-02